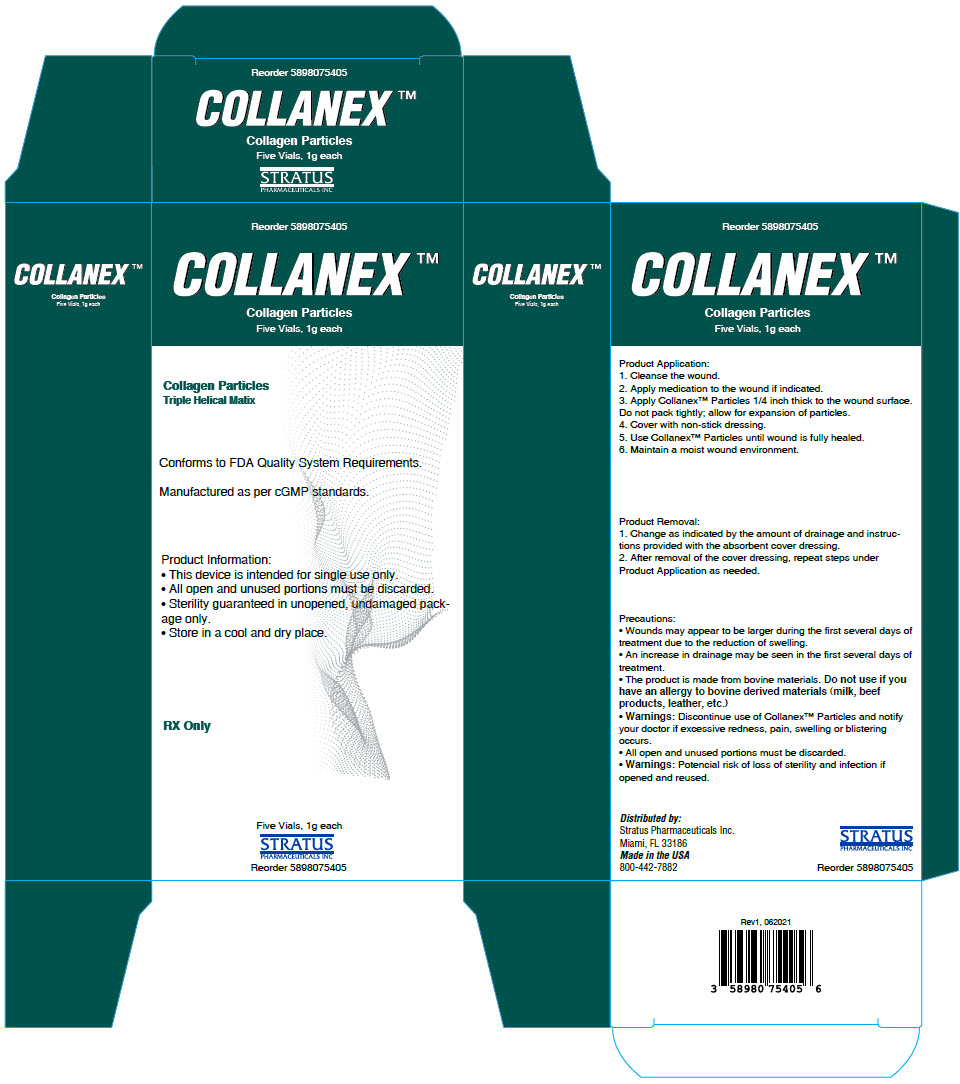 DRUG LABEL: Collanex Collagen Particles 
NDC: 58980-754 | Form: POWDER
Manufacturer: STRATUS PHARMACEUTICALS INC
Category: other | Type: MEDICAL DEVICE
Date: 20211129

ACTIVE INGREDIENTS: BOVINE TYPE I COLLAGEN 1 g/1 1

COLLANEX™
Collagen Particles

Five Vials, 1g each

Collagen Particles
Triple Helical Matix

Conforms to FDA Quality System Requirements.

Manufactured as per cGMP standards.

Product Information

- This device is intended for single use only.
- All open and unused portions must be discarded.
- Sterility guaranteed in unopened, undamaged package only.
- Store in a cool and dry place.

Product Application

1. Cleanse the wound.
2. Apply medication to the wound if indicated.
3. Apply Collanex™ Particles 1/4 inch thick to the wound surface. Do not pack tightly; allow for expansion of particles.
4. Cover with non-stick dressing.
5. Use Collanex™ Particles until wound is fully healed.
6. Maintain a moist wound environment.

Product Removal

1. Change as indicated by the amount of drainage and instructions provided with the absorbent cover dressing.
2. After removal of the cover dressing, repeat steps under Product Application as needed.

Precautions

- Wounds may appear to be larger during the first several days of treatment due to the reduction of swelling.
- An increase in drainage may be seen in the first several days of treatment.
- The product is made from bovine materials. Do not use if you have an allergy to bovine derived materials (milk, beef products, leather, etc.)
- Warnings: Discontinue use of Collanex™ Particles and notify your doctor if excessive redness, pain, swelling or blistering occurs.
- All open and unused portions must be discarded.
- Warnings: Potencial risk of loss of sterility and infection if opened and reused.

RX Only

Distributed by:
Stratus Pharmaceuticals Inc.
Miami, FL 33186
Made in the USA
800-442-7882

STRATUS
PHARMACEUTICALS INC

Reorder 5898075405

Rev1, 062021

PRINCIPAL DISPLAY PANEL - 1 g Vial Carton

COLLANEX™
Collagen Particles
Five Vials, 1g each

Collagen Particles
Triple Helical Matix

Conforms to FDA Quality System Requirements.

Manufactured as per cGMP standards.

Product Information:

- This device is intended for single use only.
- All open and unused portions must be discarded.
- Sterility guaranteed in unopened, undamaged pack-
  age only.
- Store in a cool and dry place.

RX Only

Five Vials, 1g each

STRATUS
PHARMACEUTICALS INC

Reorder 5898075405